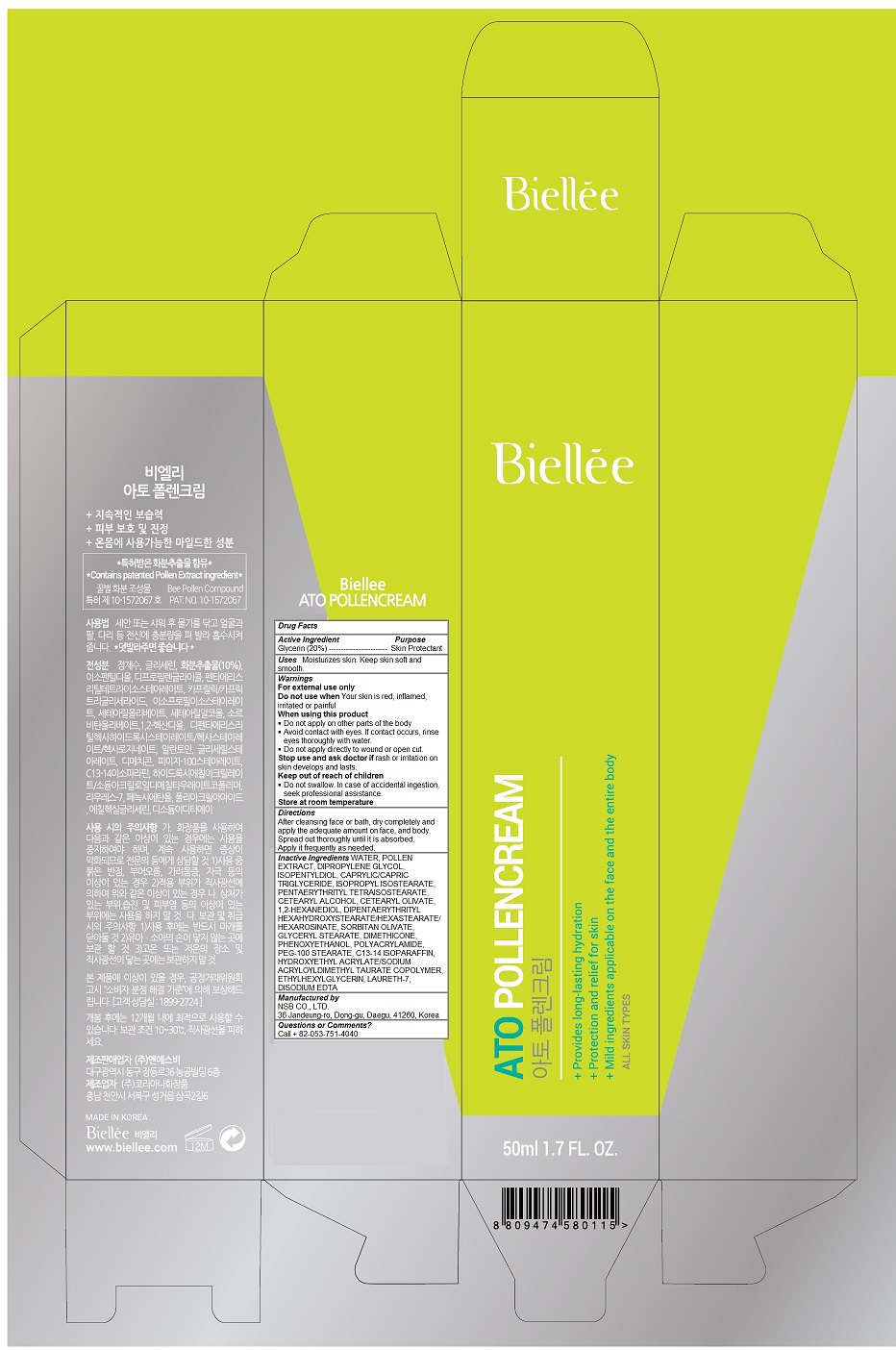 DRUG LABEL: Ato Pollen
NDC: 70784-005 | Form: CREAM
Manufacturer: NSB Co., Ltd.
Category: otc | Type: HUMAN OTC DRUG LABEL
Date: 20190107

ACTIVE INGREDIENTS: GLYCERIN 10 g/50 mL
INACTIVE INGREDIENTS: WATER; BEE POLLEN; DIPROPYLENE GLYCOL; ISOPENTYLDIOL; MEDIUM-CHAIN TRIGLYCERIDES; ISOPROPYL ISOSTEARATE; PENTAERYTHRITYL TETRAISOSTEARATE; CETOSTEARYL ALCOHOL; CETEARYL OLIVATE; 1,2-HEXANEDIOL; DIPENTAERYTHRITYL HEXAHYDROXYSTEARATE; SORBITAN OLIVATE; GLYCERYL MONOSTEARATE; DIMETHICONE; PHENOXYETHANOL; POLYACRYLAMIDE (10000 MW); PEG-100 STEARATE; C13-14 ISOPARAFFIN; HYDROXYETHYL ACRYLATE/SODIUM ACRYLOYLDIMETHYL TAURATE COPOLYMER (100000 MPA.S AT 1.5%); ETHYLHEXYLGLYCERIN; LAURETH-7; EDETATE DISODIUM

Ato Pollen Cream

Active Ingredients

Glycerin (20%)

Purpose

Skin Protectant

Keep out of reach of children

Do not swallow. In case of accidental ingestion, seek professional assistance

Uses

Moisturizes skin. Keep skin soft and smooth

Directions

After cleansing face or bath, dry completely and apply the adequate amount on face, and body. Spread out thoroughly until it is absorbed. Apply it frequently as needed.

Inactive Ingredients

WATER, POLLEN EXTRACT, DIPROPYLENE GLYCOL, ISOPENTYLDIOL, CAPRYLIC/CAPRIC TRIGLYCERIDE, ISOPROPYL ISOSTEARATE, PENTAERYTHRITYL TETRAISOSTEARATE, CETEARYL ALCOHOL, CETEARYL OLIVATE, 1,2-HEXANEDIOL, DIPENTAERYTHRITYL HEXAHYDROXYSTEARATE/HEXASTEARATE/HEXAROSINATE, SORBITAN OLIVATE, GLYCERYL STEARATE, DIMETHICONE, PHENOXYETHANOL, POLYACRYLAMIDE, PEG-100 STEARATE, C13-14 ISOPARAFFIN, HYDROXYETHYL ACRYLATE/SODIUM ACRYLOYLDIMETHYL TAURATE COPOLYMER, ETHYLHEXYLGLYCERIN, LAURETH-7, DISODIUM EDTA

Warnings

For external use only
Do not use when Your skin is red, inflamed, irritated or painful
When using this product
 Do not apply on other parts of the body
 Avoid contact with eyes. If contact occurs, rinse eyes thoroughly with water.
 Do not apply directly to wound or open cut.
Stop use and ask doctor if rash or irritation on skin develops and lasts.

Store at room temperature